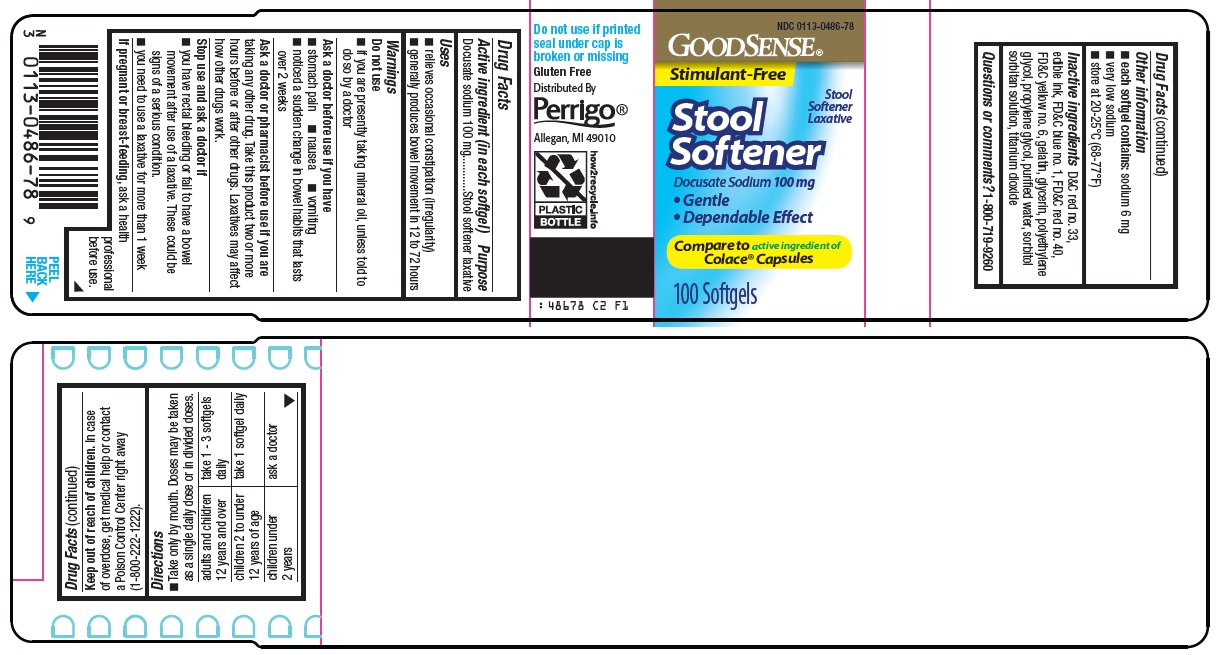 DRUG LABEL: good sense stool softener
NDC: 0113-0486 | Form: CAPSULE, LIQUID FILLED
Manufacturer: L. Perrigo Company
Category: otc | Type: HUMAN OTC DRUG LABEL
Date: 20251114

ACTIVE INGREDIENTS: DOCUSATE SODIUM 100 mg/1 1
INACTIVE INGREDIENTS: D&C RED NO. 33; FD&C BLUE NO. 1; FD&C RED NO. 40; FD&C YELLOW NO. 6; GELATIN, UNSPECIFIED; GLYCERIN; POLYETHYLENE GLYCOL, UNSPECIFIED; PROPYLENE GLYCOL; WATER; SORBITOL SOLUTION; SORBITAN; TITANIUM DIOXIDE

Perrigo Stool Softener Drug Facts

Active ingredient (in each softgel)

Docusate sodium 100 mg

Purpose

Stool softener laxative

Uses

1. relieves occasional constipation (irregularity)
2. generally produces bowel movement in 12 to 72 hours

Warnings

Do not use

- if you are presently taking mineral oil, unless told to do so by a doctor

Ask a doctor before use if you have

1. stomach pain
2. nausea
3. vomiting
4. noticed a sudden change in bowel habits that lasts over 2 weeks

Ask a doctor or pharmacist before use if you are

taking any other drug. Take this product two or more hours before or after other drugs. Laxatives may affect how other drugs work.

Stop use and ask a doctor if

1. you have rectal bleeding or fail to have a bowel movement after use of a laxative. These could be signs of a serious condition.
2. you need to use a laxative for more than 1 week

If pregnant or breast-feeding,

ask a health professional before use.

Keep out of reach of children.

In case of overdose, get medical help or contact a Poison Control Center right away. (1-800-222-1222)

Directions

1. Take only by mouth. Doses may be taken as a single daily dose or in divided doses.

adults and children 12 years and over | take 1 - 3 softgels daily
children 2 to under 12 years of age | take 1 softgel daily
children under 2 years | ask a doctor

Other information

1. each softgel contains: sodium 6 mg
2. very low sodium
3. store at 20-25°C (68-77°F)

Inactive ingredients

D&C red no. 33, edible ink, FD&C blue no. 1, FD&C red no. 40, FD&C yellow no. 6, gelatin, glycerin, polyethylene glycol, propylene glycol, purified water, sorbitol sorbitan solution, titanium dioxide

Questions or comments?

1-800-719-9260

Principal Display Panel

GOODSENSE®

Stimulant-Free

Stool Softener Laxative

Stool Softener

Docusate Sodium 100 mg

• Gentle

• Dependable Effect

Compare to active ingredient of Colace® Capsules

100 Softgels